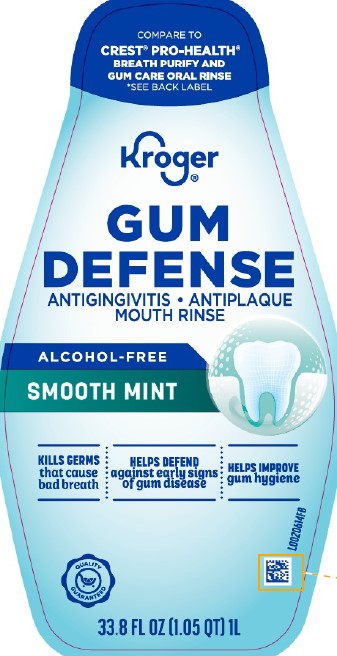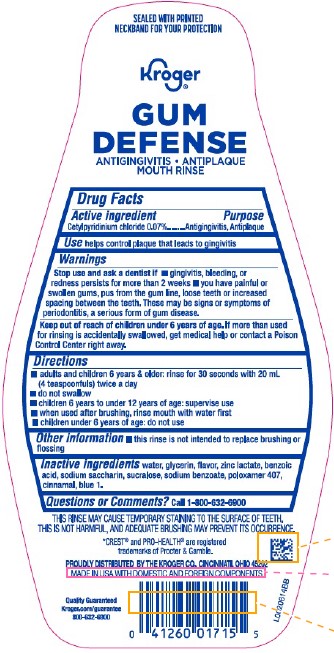 DRUG LABEL: Antigingivitis/Antiplaque
NDC: 59450-997 | Form: MOUTHWASH
Manufacturer: The Kroger Co.
Category: otc | Type: HUMAN OTC DRUG LABEL
Date: 20260227

ACTIVE INGREDIENTS: CETYLPYRIDINIUM CHLORIDE 0.7 mg/1 mL
INACTIVE INGREDIENTS: WATER; GLYCERIN; ZINC LACTATE; BENZOIC ACID; SACCHARIN SODIUM; SUCRALOSE; SODIUM BENZOATE; POLOXAMER 407; CINNAMALDEHYDE; FD&C BLUE NO. 1

Kroger D00.001/D00AA
Alcohol-Free Gum Defense Mouthwash

Tamper Evident Statement

SEALED WITH PRINTED NECKBAND FOR YOUR PROTECTION

Claims

Kroger®

GUM DEFENSE

ANTIGINGIVITIS

ANTIPLAQUE

MOUTH RINSE

Active Ingredient

Cetylpyridinium Chloride 0.07%

Purpose

Antigingivitis, Antiplaque

Use

helps control plaque that leads to gingivitis

Warnings

For this product

Stop use and ask a dentist if

- gingivitis, bleeding, or redness persists for more than 2 weeks
- you have painful or swollen gums, pus from the gum line, loose teeth or increased spacing between the teeth. These may be signs or symptoms of periodontitis, a serious form of gum disease.

Keep out of reach of children under 6 years of age.

If more than used for rinsing is accidentally swallowed, get medical help or contact a Poison Control Center right away.

Directions

- adults and children 6 years & older: rinse for 30 seconds with 20 mL (4 teaspoonfuls) twice a day
- do not swallow
- children 6 years to under 12 years of age: supervise use
- when used after brushing, rinse mouth with water first
- children under 6 years of age: do not use

Other information

- this rinse is not intended to replace brushing or flossing

Inactive ingredients

water, glycerin, flavor, zinc lactate, benzoic acid, sodium saccharin, sucralose, sodium benzoate, poloxamer 407, cinnamal, blue 1

Questions or Comments?

Call 1-800-632-6900

Disclaimers

This may cause temporary staining to the surface of teeth.

This is not harmful, and adequate brushing may prevent its occurrence.

*Crest® and Pro-Health® are registered trademarks of the Proctor & Gamble Co.

ADVERSE REACTION

PROUDLY DISTRIBUTED BY THE KROGER CO., CINCINNATI, OH 45202

MADE IN USA WITH DOMESTIC AND FOREIGN COMPONENTS.

Quality Guaranteed

Kroger.com/guarantee 800-632-6900

Principal Panel Display

COMPARE TOCREST®PRO-HEALTH® BREATHPURIFY AND GUM CARE ORAL RINSE

SEE BACK LABEL*

Kroger®

GUM DEFENSE

ANTIGINGIVITIS • ANTIPLAQUE

MOUTH RINSE

ALCOHOL-FREE

SMOOTH MINT

KILLS GERMS THAT CAUSE BAD BREATH

HELPS DEFEND AGAINST EARLY SIGNS OF GUM DISEASE

HELPS IMPROVE GUM HYGIENE

QUALITY GUARANTEED

33.8 FL OZ (1.05 QT) 1 L